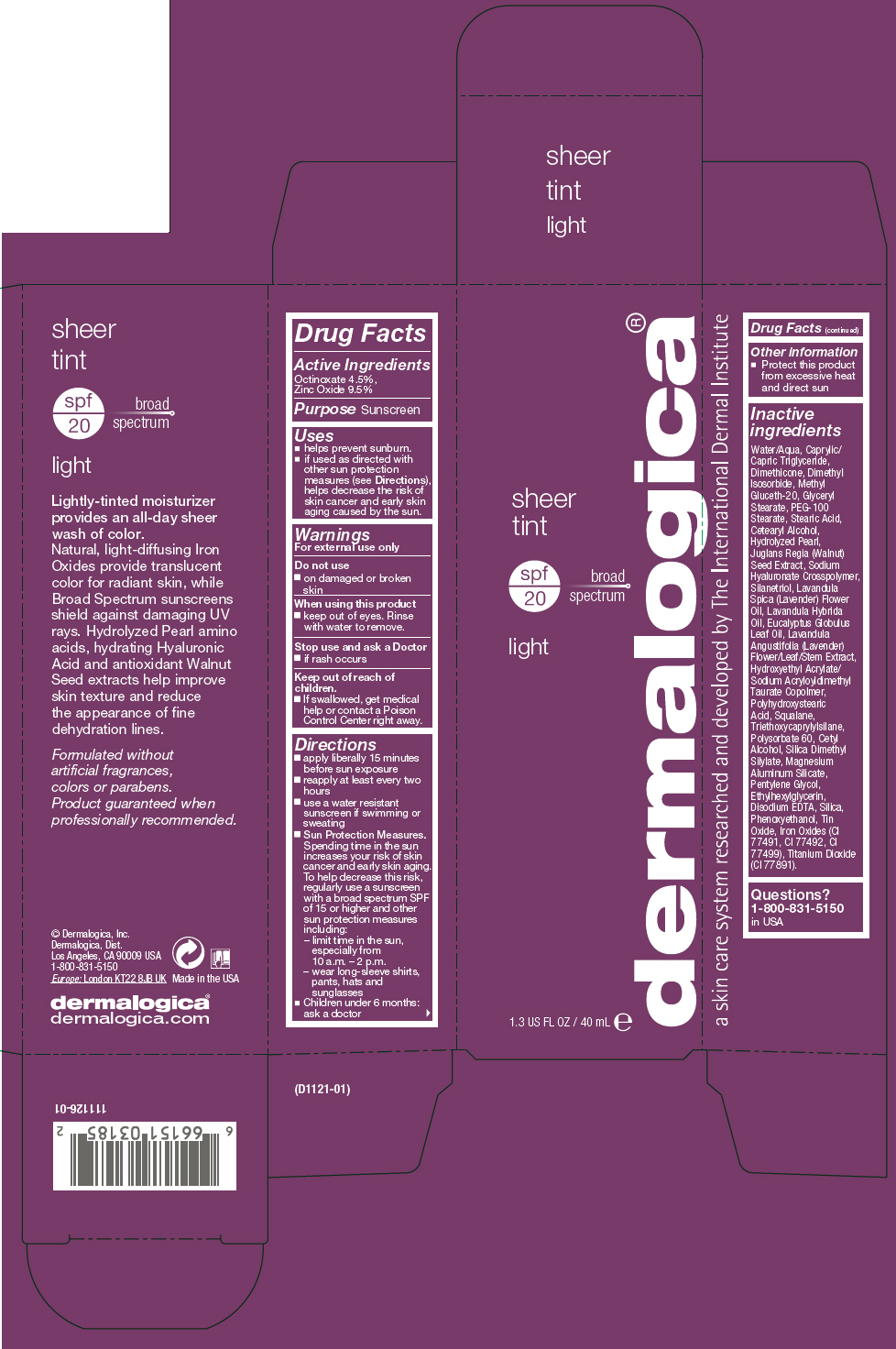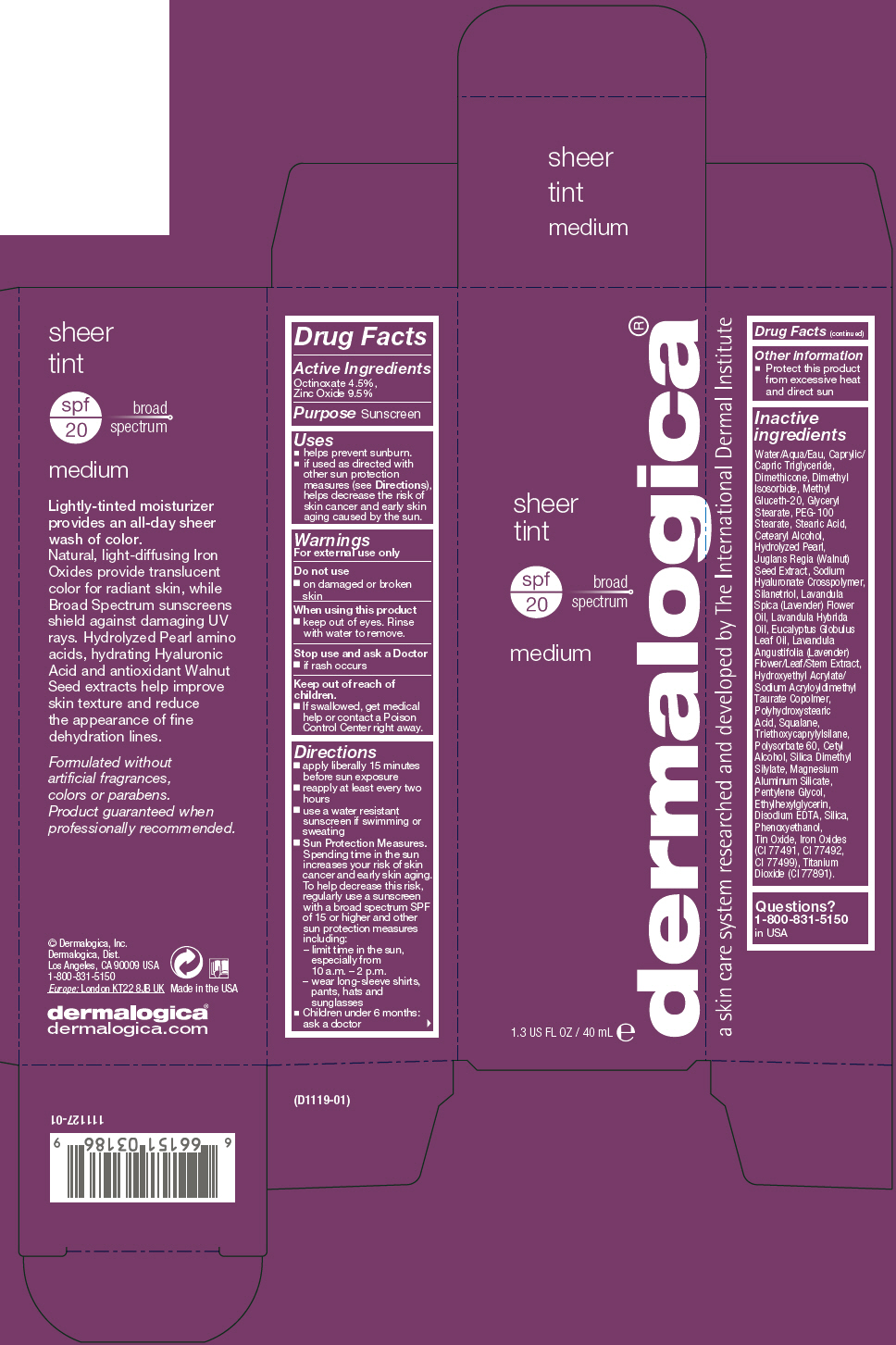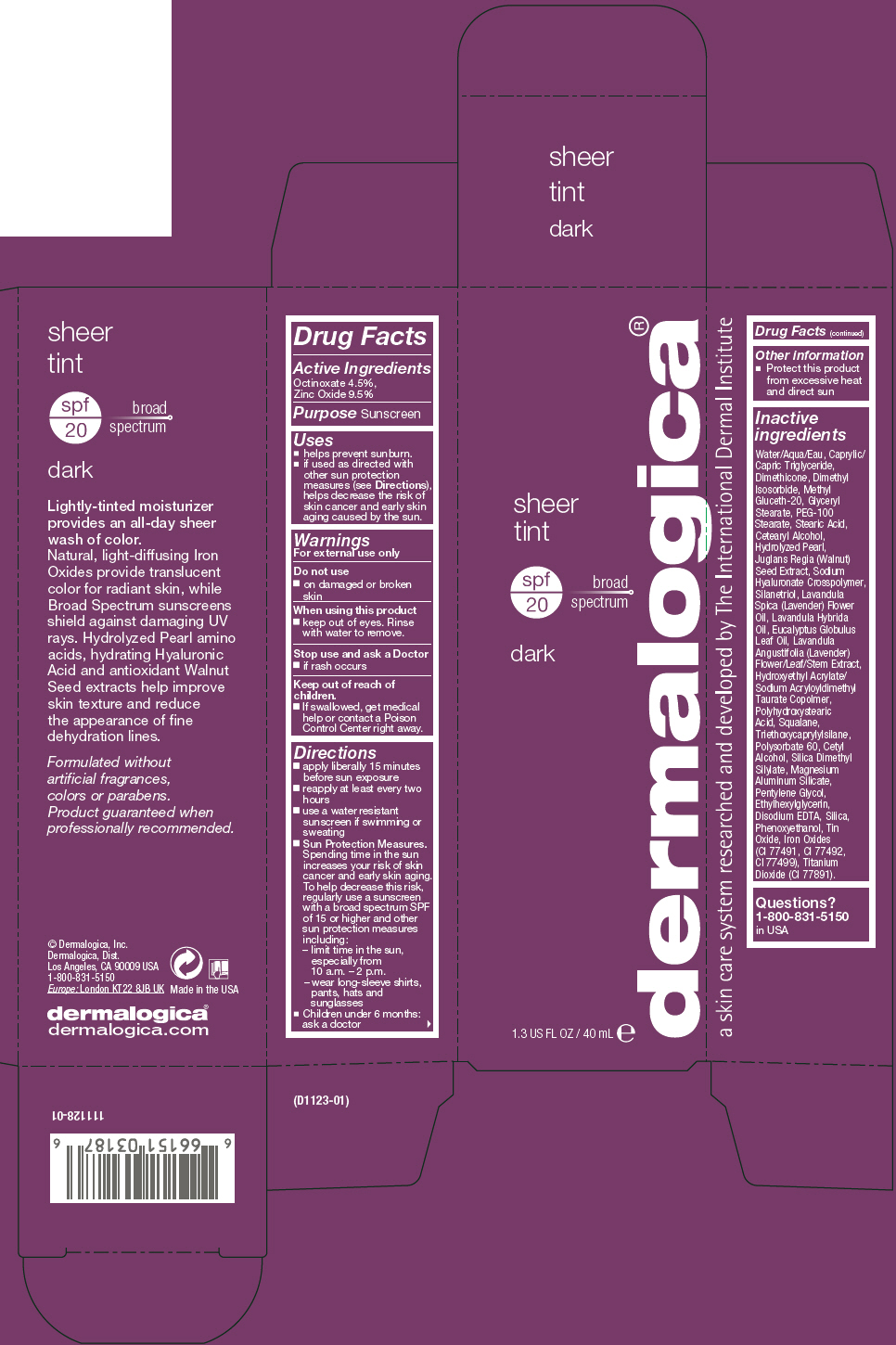 DRUG LABEL: Sheer Tint 
NDC: 68479-201 | Form: LOTION
Manufacturer: Dermalogica, Inc.
Category: otc | Type: HUMAN OTC DRUG LABEL
Date: 20171204

ACTIVE INGREDIENTS: Zinc Oxide 95 mg/1 mL; Octinoxate 45 mg/1 mL
INACTIVE INGREDIENTS: Water; Medium-Chain Triglycerides; Dimethicone; Dimethyl Isosorbide; Methyl Gluceth-20; Glyceryl Monostearate; PEG-100 Stearate; Stearic Acid; Cetostearyl Alcohol; Calcium Carbonate; English Walnut; PEG-9 Diglycidyl Ether/Sodium Hyaluronate Crosspolymer; Silanetriol; Lavender Oil; Lavandin Oil; Eucalyptus Oil; LAVANDULA ANGUSTIFOLIA SUBSP. ANGUSTIFOLIA FLOWERING TOP; Hydroxyethyl Acrylate/Sodium Acryloyldimethyl Taurate Copolymer (100000 MPA.S at 1.5%); Polyhydroxystearic Acid (2300 MW); Squalane; Triethoxycaprylylsilane; Polysorbate 60; Cetyl Alcohol; Silica Dimethyl Silylate; Magnesium Aluminum Silicate; Pentylene Glycol; Ethylhexylglycerin; Edetate Disodium; Silicon Dioxide; Phenoxyethanol; Stannic Oxide; Ferric Oxide Red; Ferric Oxide Yellow; Ferrosoferric Oxide; Titanium Dioxide

Sheer Tint
SPF20

Drug Facts

Active Ingredients

Octinoxate 4.5%,
Zinc Oxide 9.5%

Purpose

Sunscreen

Uses

- helps prevent sunburn.
- if used as directed with other sun protection measures (see Directions), helps decrease the risk of skin cancer and early skin aging caused by the sun.

Warnings

For external use only

Do not use

- on damaged or broken skin

When using this product

- keep out of eyes. Rinse with water to remove.

Stop use and ask a Doctor

- if rash occurs

Keep out of reach of children.

- If swallowed, get medical help or contact a Poison Control Center right away.

Directions

- apply liberally 15 minutes before sun exposure
- reapply at least every two hours
- use a water resistant sunscreen if swimming or sweating
- Sun Protection Measures. Spending time in the sun increases your risk of skin cancer and early skin aging. To help decrease this risk, regularly use a sunscreen with a broad spectrum SPF of 15 or higher and other sun protection measures including:
  - limit time in the sun, especially from 10 a.m. – 2 p.m.
  - wear long-sleeve shirts, pants, hats and sunglasses
- Children under 6 months: ask a doctor

Other information

- Protect this product from excessive heat and direct sun

Inactive ingredients

Water/Aqua, Caprylic/Capric Triglyceride, Dimethicone, Dimethyl Isosorbide, Methyl Gluceth-20, Glyceryl Stearate, PEG-100 Stearate, Stearic Acid, Cetearyl Alcohol, Hydrolyzed Pearl, Juglans Regia (Walnut) Seed Extract, Sodium Hyaluronate Crosspolymer, Silanetriol, Lavandula Spica (Lavender) Flower Oil, Lavandula Hybrida Oil, Eucalyptus Globulus Leaf Oil, Lavandula Angustifolia (Lavender) Flower/Leaf/Stem Extract, Hydroxyethyl Acrylate/ Sodium Acryloyldimethyl Taurate Copolmer, Polyhydroxystearic Acid, Squalane, Triethoxycaprylylsilane, Polysorbate 60, Cetyl Alcohol, Silica Dimethyl Silylate, Magnesium Aluminum Silicate, Pentylene Glycol, Ethylhexylglycerin, Disodium EDTA, Silica, Phenoxyethanol, Tin Oxide, Iron Oxides (CI 77491, CI 77492, CI 77499), Titanium Dioxide (CI 77891).

Questions?

1-800-831-5150 in USA

PRINCIPAL DISPLAY PANEL - 40 mL Tube Carton - Light

sheer
tint

spf
20

broad
spectrum

light

1.3 US FL OZ / 40 mL e

dermalogica®

PRINCIPAL DISPLAY PANEL - 40 mL Tube Carton - Medium

sheer
tint

spf
20

broad
spectrum

medium

1.3 US FL OZ / 40 mL e

dermalogica®

PRINCIPAL DISPLAY PANEL - 40 mL Tube Carton - Dark

sheer
tint

spf
20

broad
spectrum

dark

1.3 US FL OZ / 40 mL e

dermalogica®